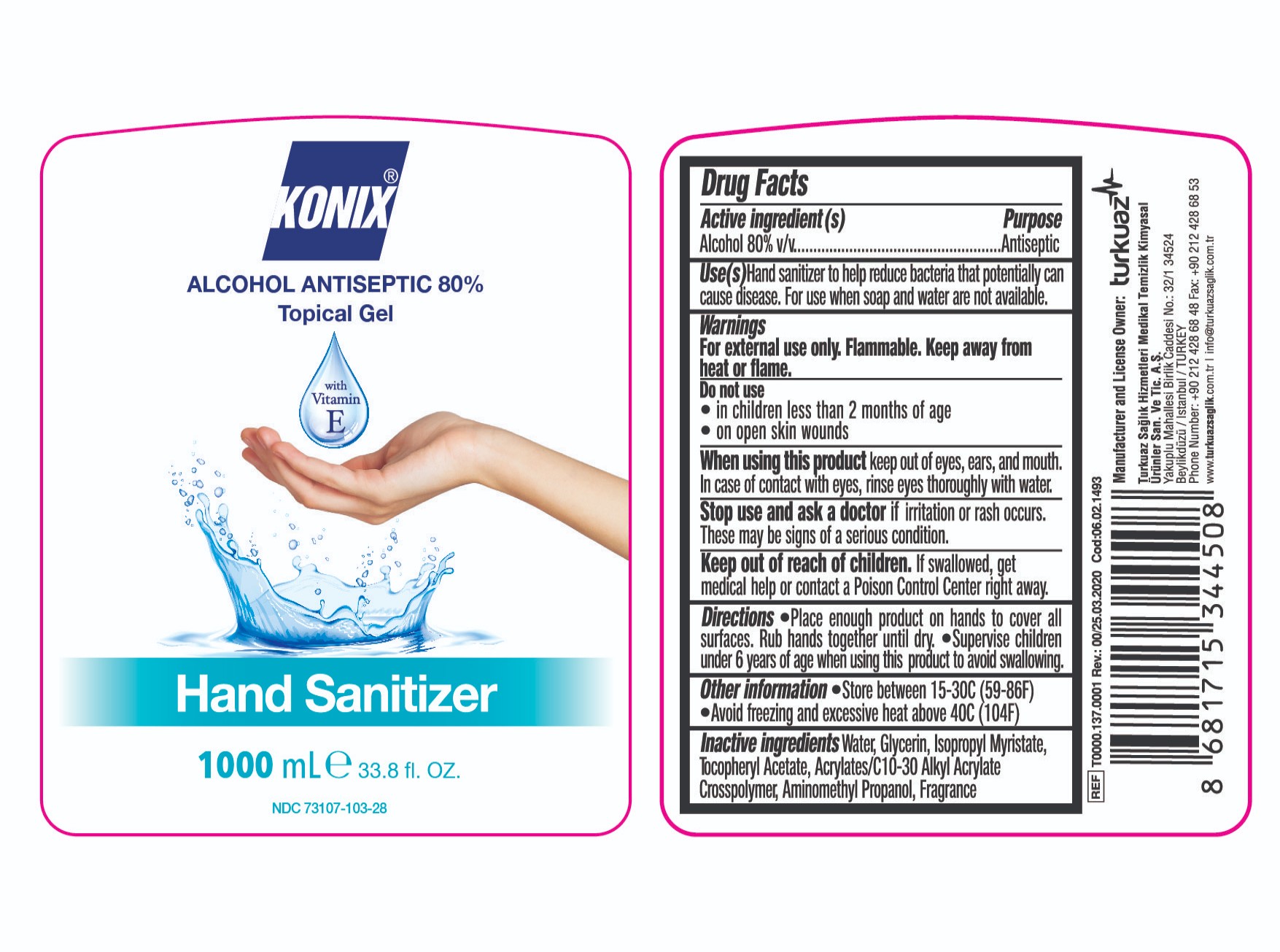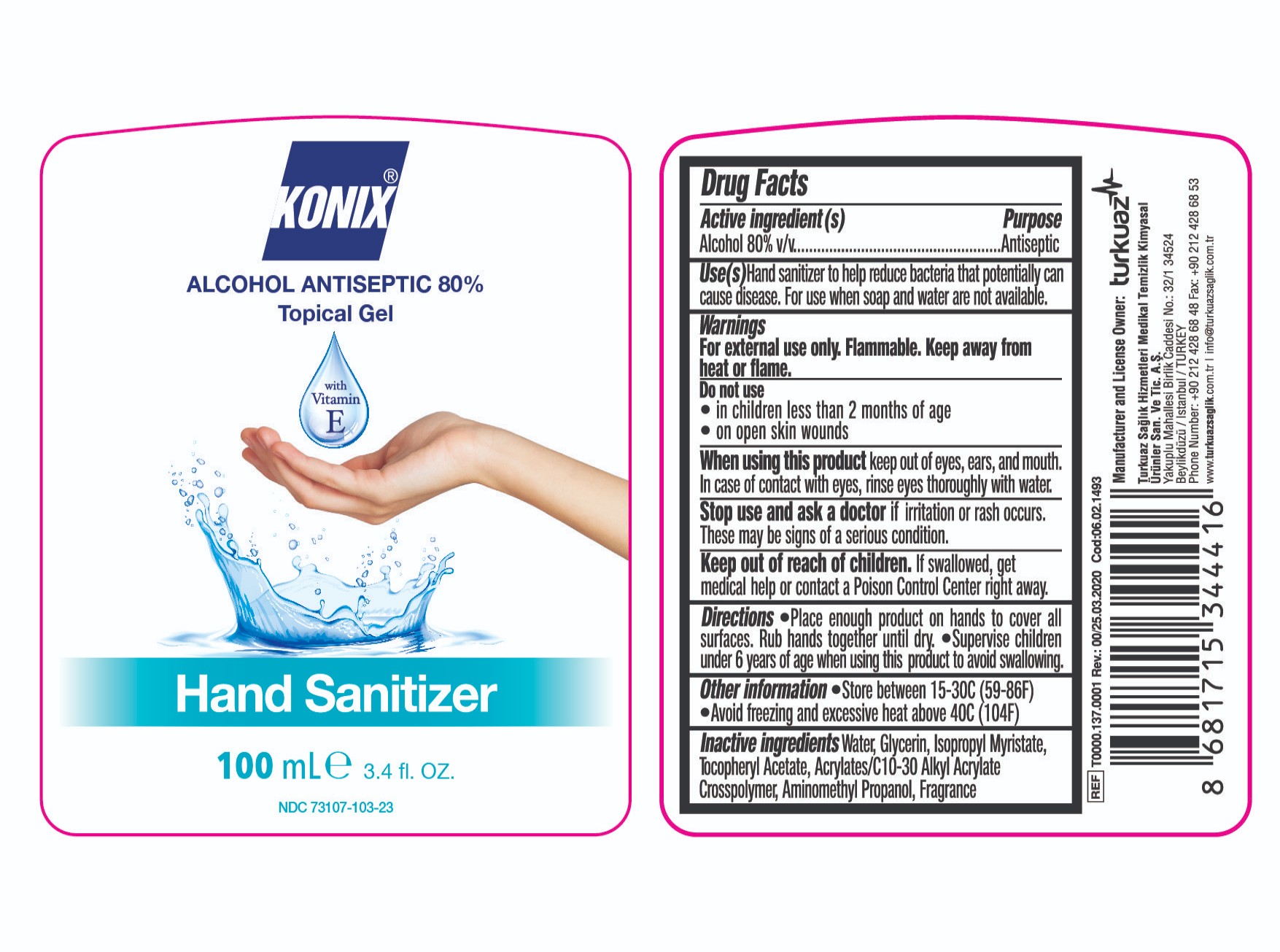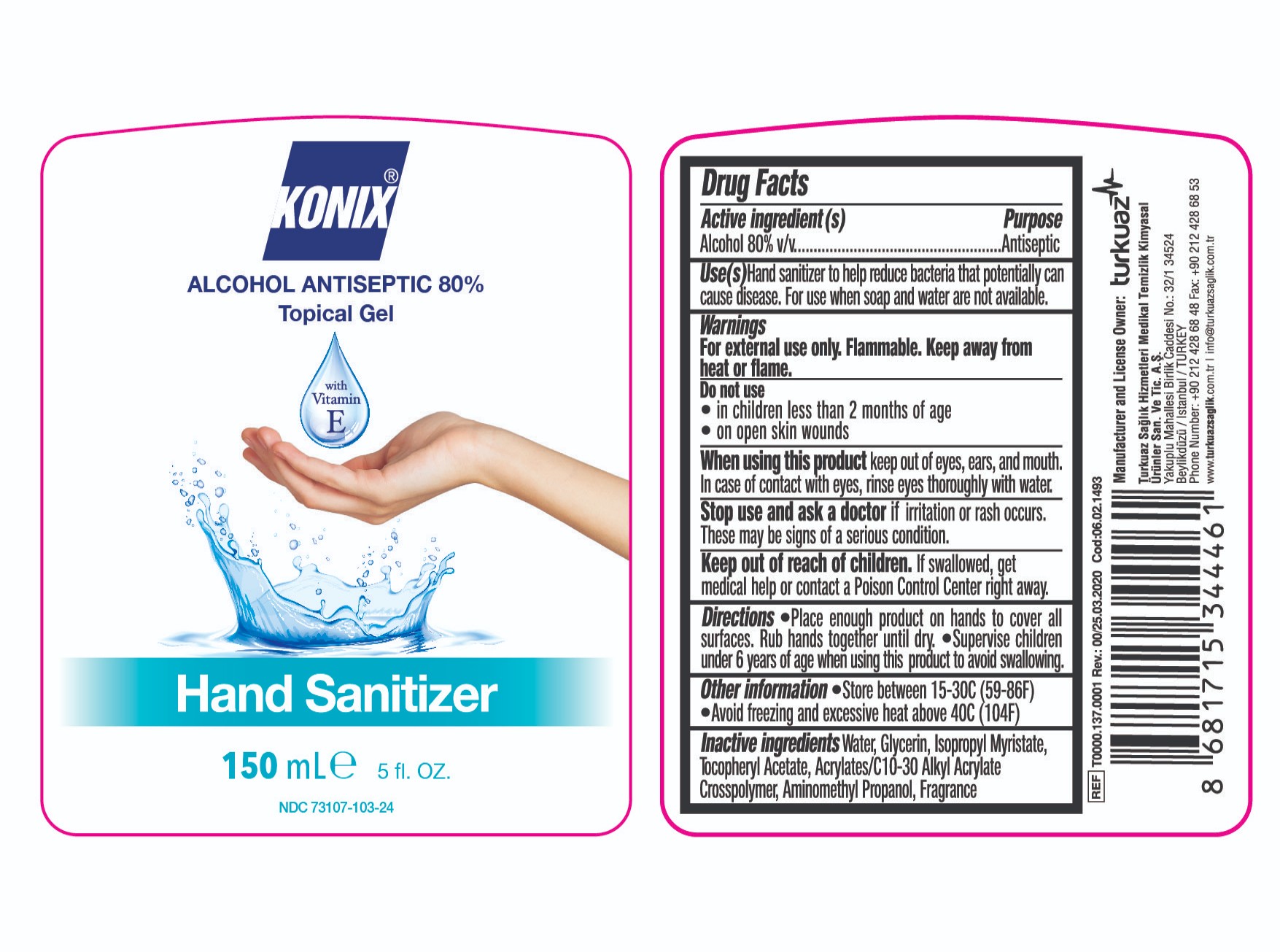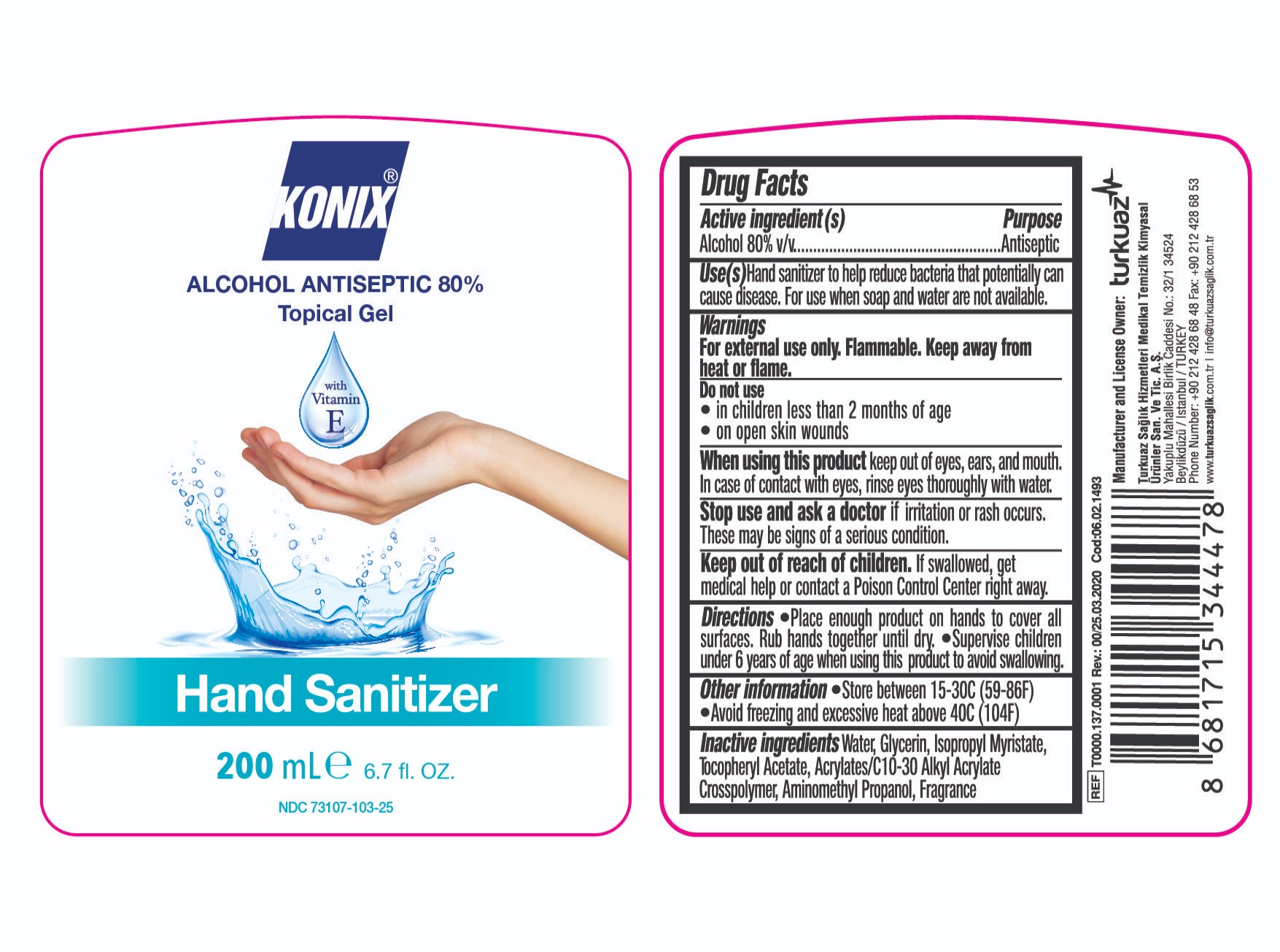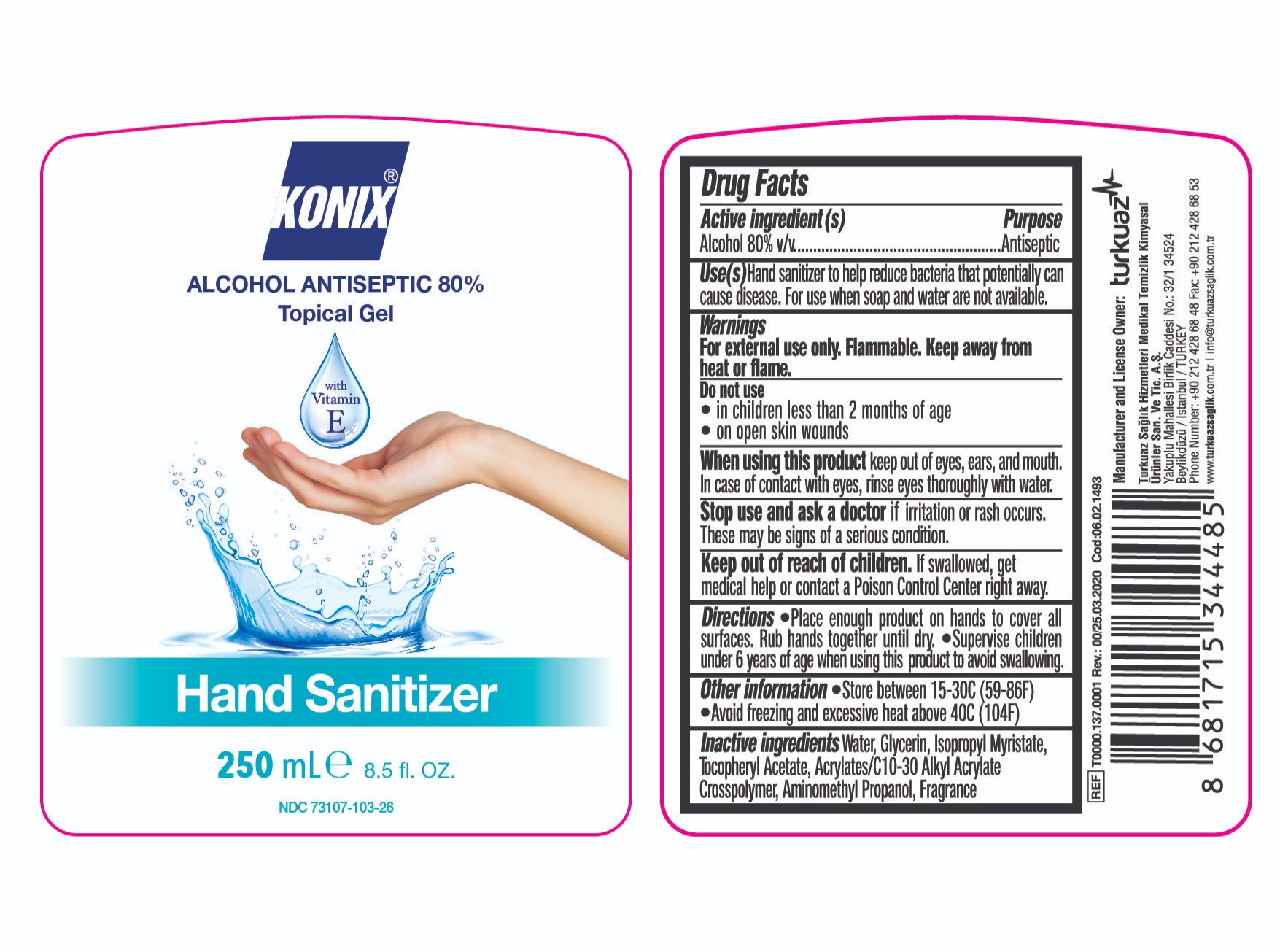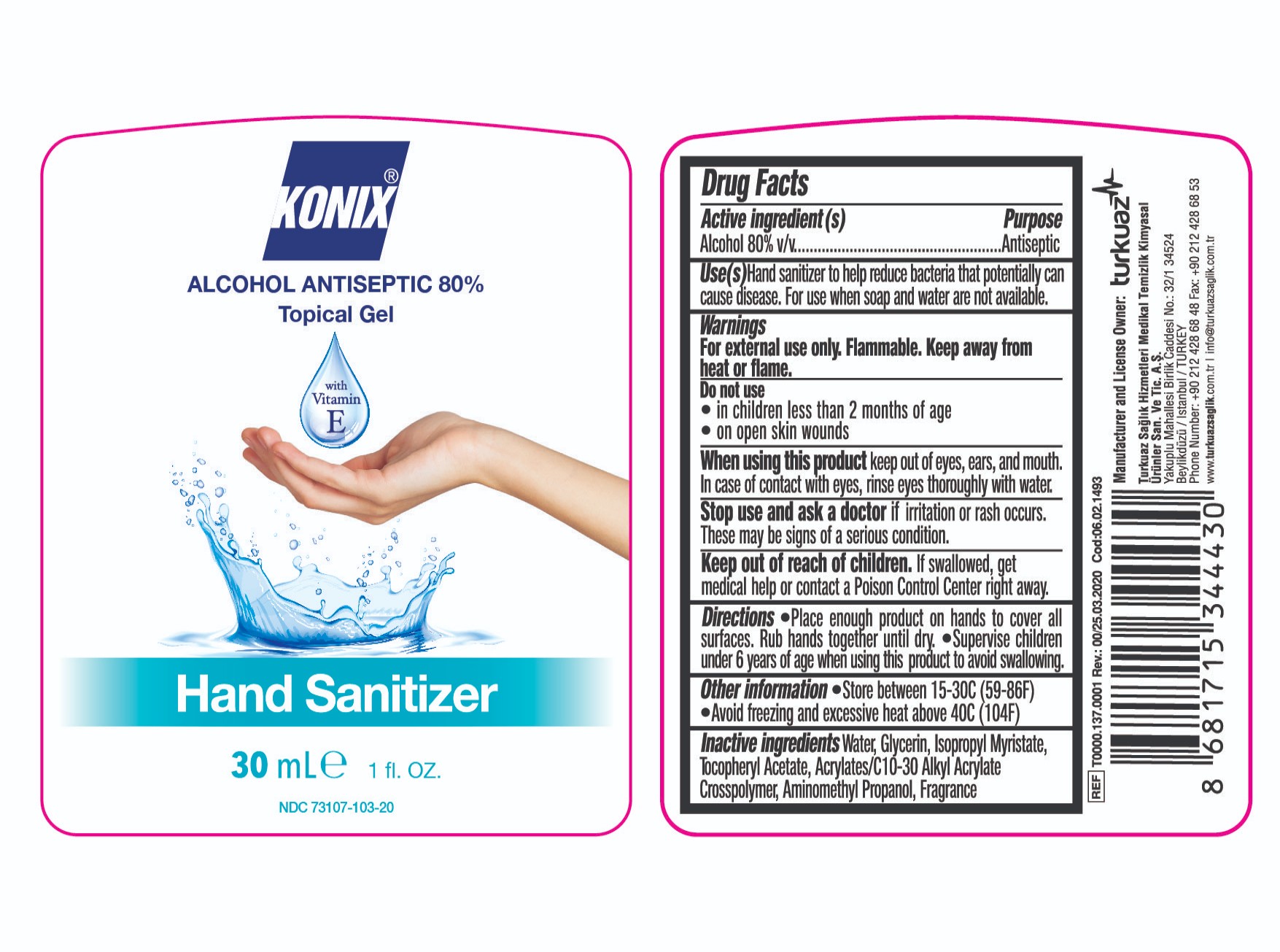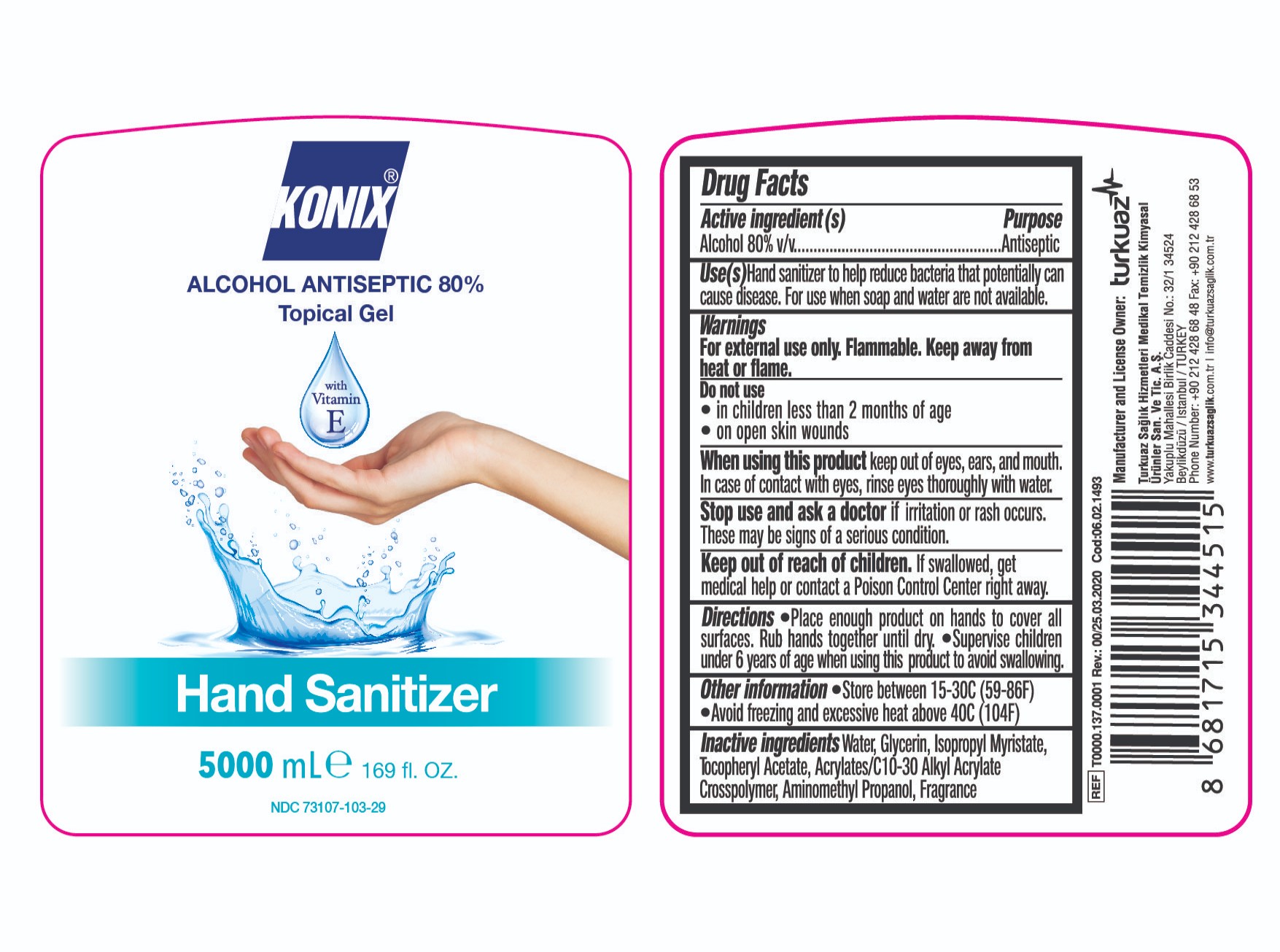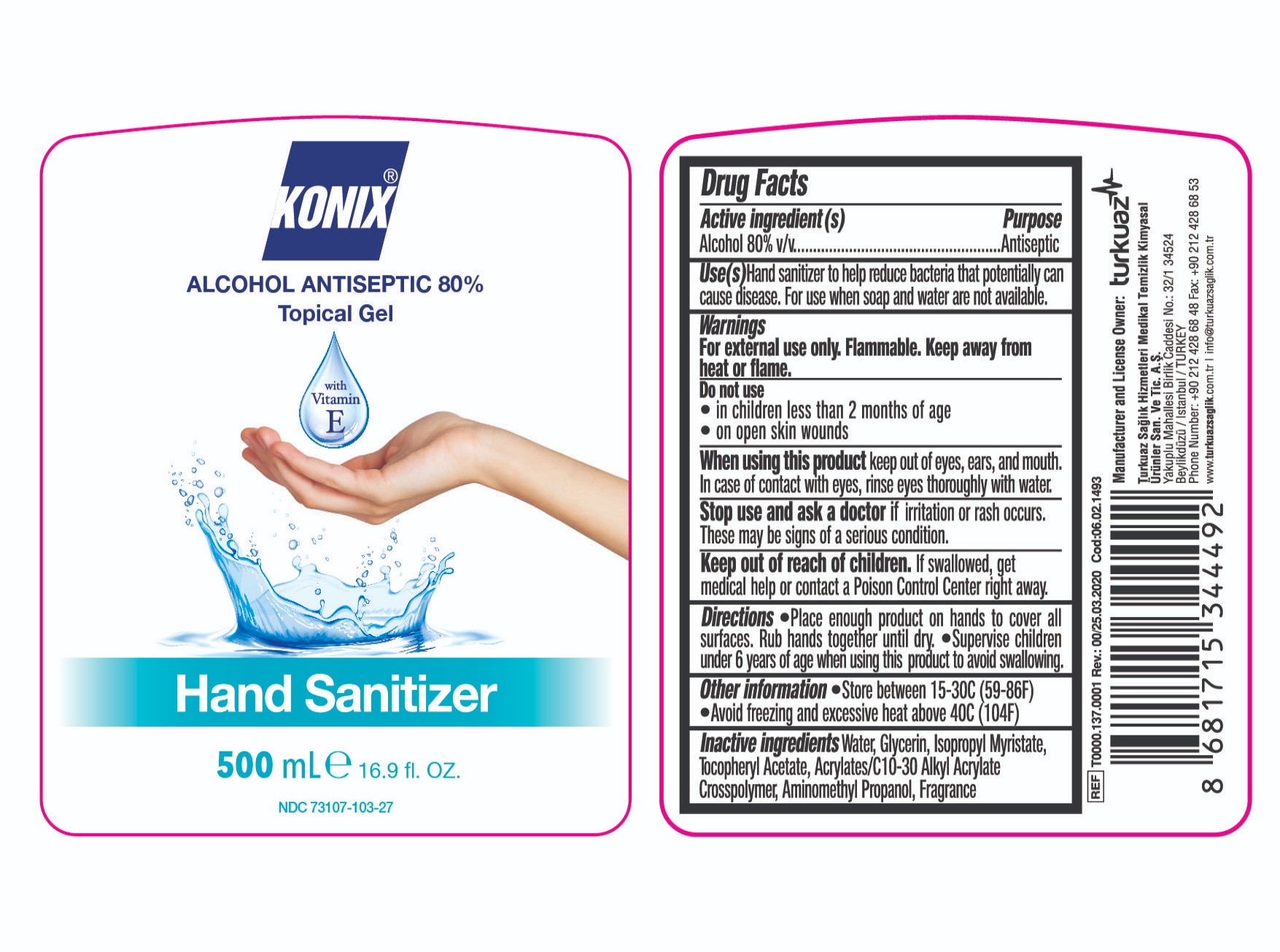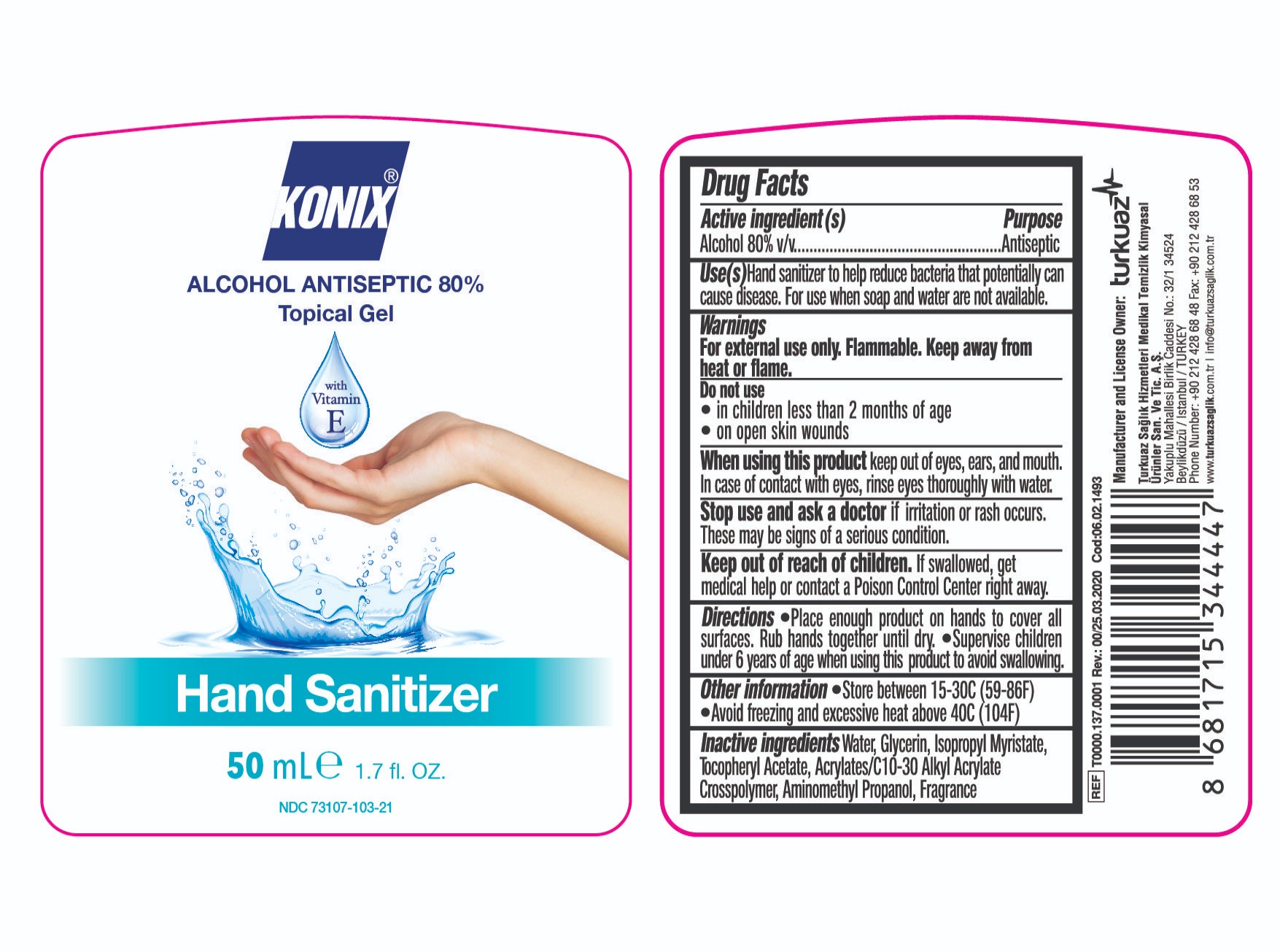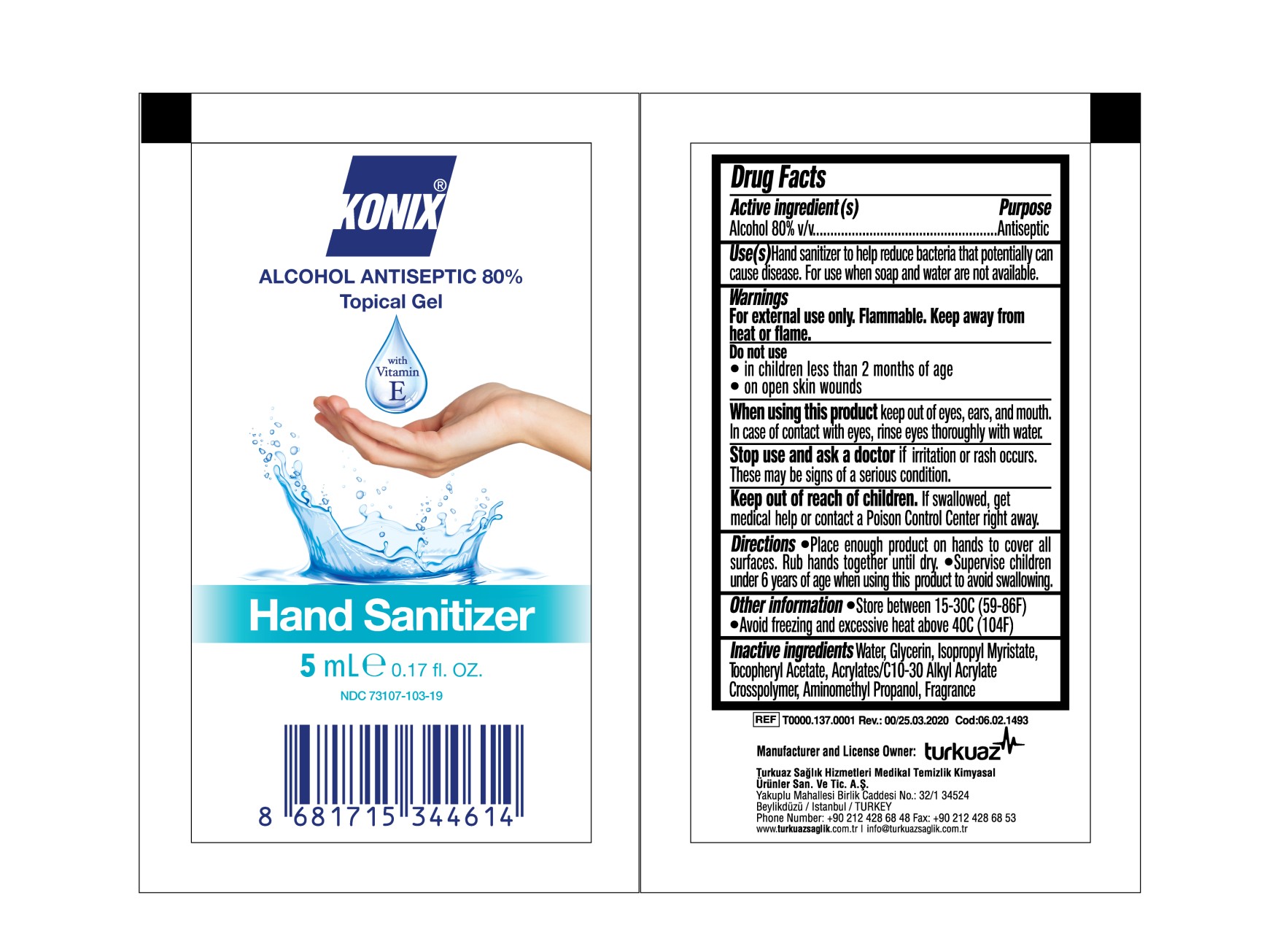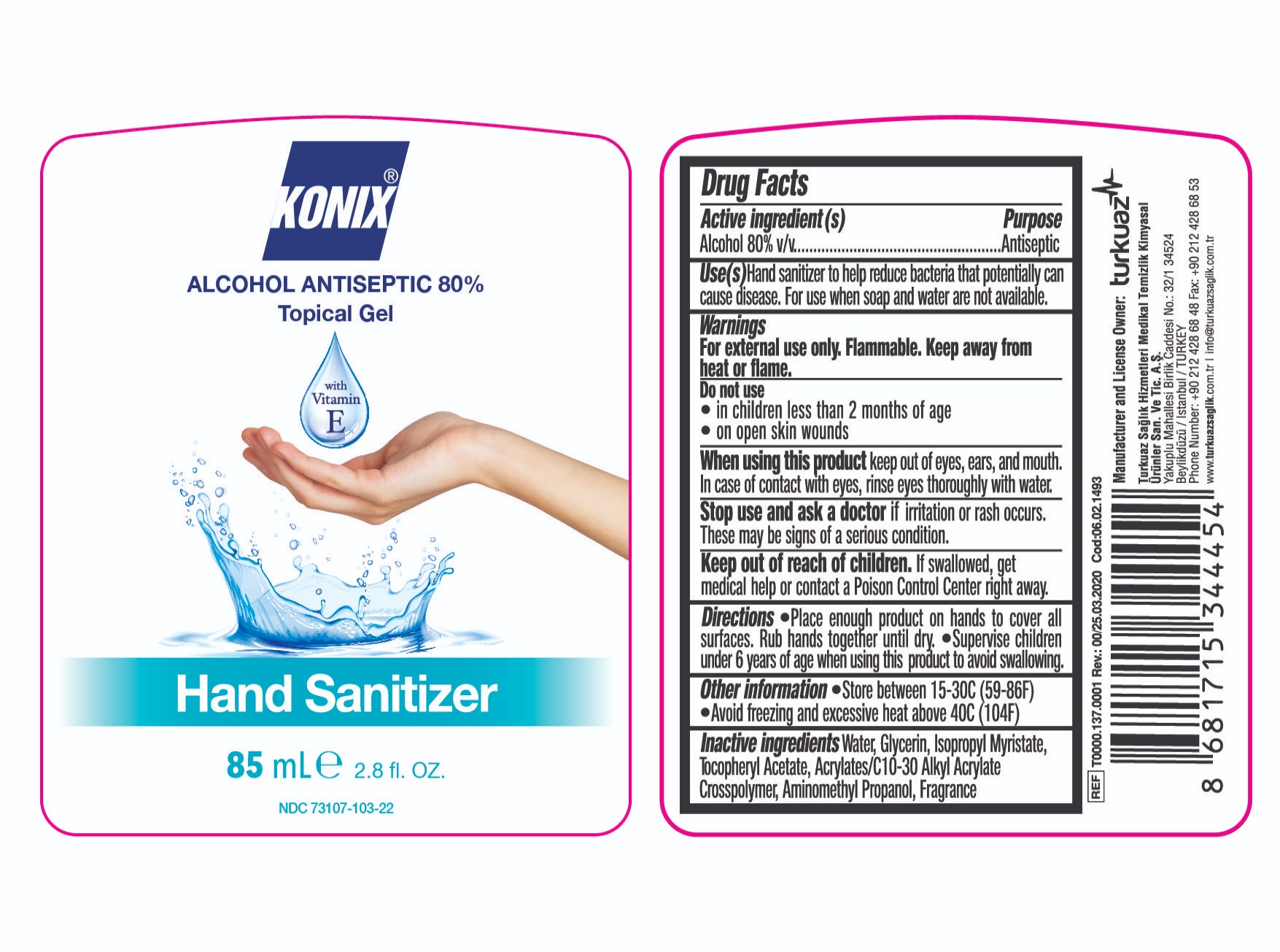 DRUG LABEL: Konix  ALCOHOL ANTISEPTIC HAND SANITIZER
NDC: 73107-103 | Form: GEL
Manufacturer: Turkuaz Saglik Hizmetleri Medikal Temizlik Kimyasal Urunler
Category: otc | Type: HUMAN OTC DRUG LABEL
Date: 20200420

ACTIVE INGREDIENTS: ALCOHOL 80 mL/100 mL
INACTIVE INGREDIENTS: WATER; GLYCERIN; ISOPROPYL MYRISTATE; .ALPHA.-TOCOPHEROL ACETATE; CARBOMER INTERPOLYMER TYPE A (ALLYL SUCROSE CROSSLINKED); AMINOMETHYLPROPANOL

KONIX ALCOHOL ANTISEPTIC 80% TOPICAL GEL HAND SANITIZER

Active Ingredient(s)

Alcohol 80% v/v

Purpose

Antiseptic, Hand Sanitizer Gel

Use

Uses to help reduce bacteria on the skin that potentially can cause disease. For use when soap and water are not available.

Warnings

For external use only: Flammable. Keep away from heat or flame.

DO NOT USE

In children less than 2 months of age
On open skin wounds

When using this product keep out of eyes, ears, and mouth. In case of contact with eyes, rinse eyes thoroughly with water.

Stop use and ask a doctor if Irritation or rash occurs. These may be signs of a serious condition.

Keep out of reach of children. If swallowed,get medical help or contact a Poison Control Center right away

Directions

- Place enough product on hands to cover all surfaces. Rub hands together until dry.
- Supervise children under 6 years of age when using this product to avoid swallowing.

Other Information

Store between 15-30C (59-86F) Avoid freezing and excessive heat above 40 C (104F)

Inactive ingredients

Water, glycerin, isopropyl myristate, tocopheryl acetate, acrylates/ c10-30 alkyl acrylate crosspolymer, aminomethyl propanol, fragrance

PACKAGE LABEL

KONIX Alcohol Antiseptic 80%
Topical Gel With Vitamin E HAND SANITIZER
5 ml

PACKAGE LABEL

KONIX Alcohol Antiseptic 80%
Topical Gel With Vitamin E HAND SANITIZER
30 ml

PACKAGE LABEL

KONIX Alcohol Antiseptic 80%
Topical Gel With Vitamin E HAND SANITIZER
50 ml

PACKAGE LABEL

KONIX Alcohol Antiseptic 80%
Topical Gel With Vitamin E HAND SANITIZER
85 ml

PACKAGE LABEL

KONIX Alcohol Antiseptic 80%
Topical Gel With Vitamin E HAND SANITIZER
100 ml

PACKAGE LABEL

KONIX Alcohol Antiseptic 80%
Topical Gel With Vitamin E HAND SANITIZER
150 ml

PACKAGE LABEL

KONIX Alcohol Antiseptic 80%
Topical Gel With Vitamin E HAND SANITIZER
200 ml

PACKAGE LABEL

KONIX Alcohol Antiseptic 80%
Topical Gel With Vitamin E HAND SANITIZER
250 ml

PACKAGE LABEL

KONIX Alcohol Antiseptic 80%
Topical Gel With Vitamin E HAND SANITIZER
500 ml

PACKAGE LABEL

KONIX Alcohol Antiseptic 80%
Topical Gel With Vitamin E HAND SANITIZER
1000 ml

PACKAGE LABEL

KONIX Alcohol Antiseptic 80%
Topical Gel With Vitamin E HAND SANITIZER
5000 ml